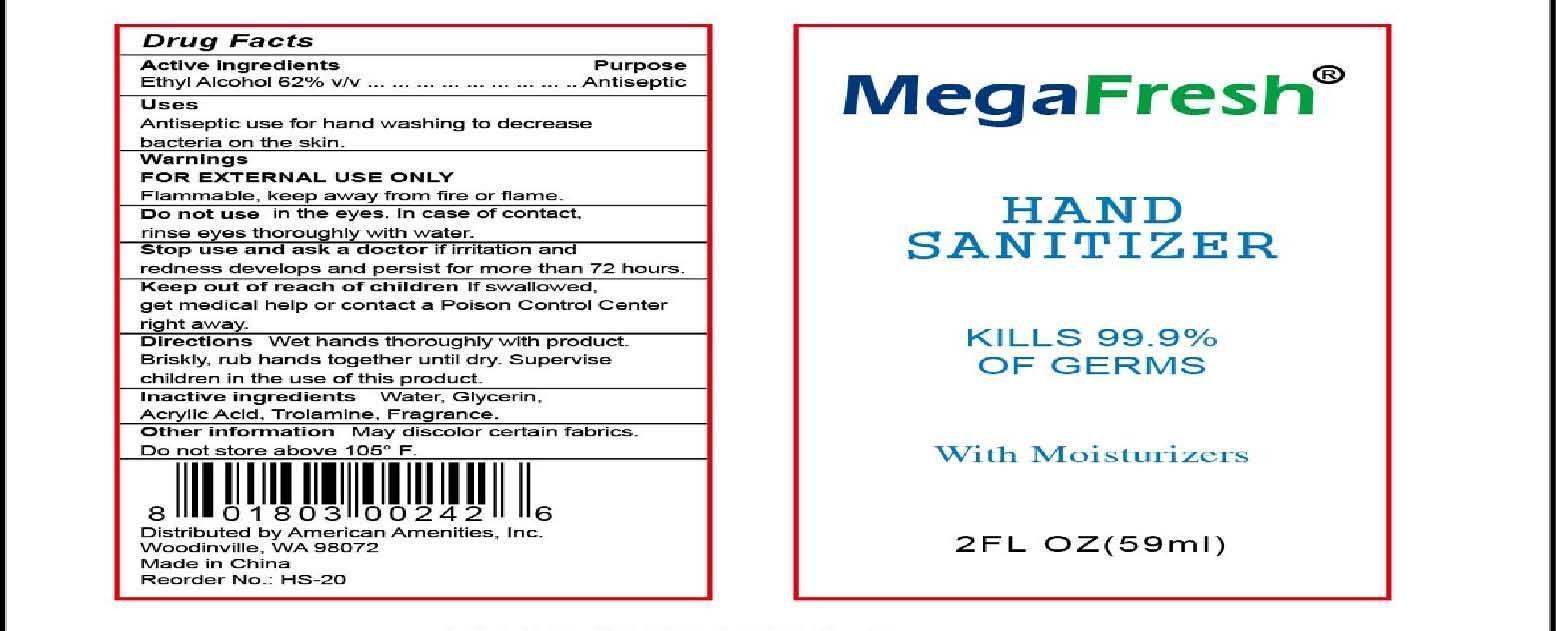 DRUG LABEL: MegaFresh Hand Sanitizer
NDC: 54157-105 | Form: LIQUID
Manufacturer: American Amenities, Inc.
Category: otc | Type: HUMAN OTC DRUG LABEL
Date: 20140816

ACTIVE INGREDIENTS: ALCOHOL 62 mL/100 mL
INACTIVE INGREDIENTS: WATER 36.70 mL/100 mL; GLYCERIN; TROLAMINE; ACRYLIC ACID

Drug Fact

Active Ingredient

Ethyl Alcohol 62% v/v

Purpose

Antiseptic

Uses

Antiseptic use for hand washing to decrease bacteria on the skin

Warnings:

For external use only.

Flammable. Keep away from fire or flame

Do not use in the eyes. In case of contact, rinse eyes throughly with water

Stop use and ask a doctor if irritation and redness develop and persist for more than 72 hours

Keep out of reach of children.

If swallowed, get medical help or contact a Poison Control Center rigth away.

Directions

Wet hands throughly with product. Briskly, rub hands together untill dry. Supervise children in the use of this product.

Inactive Ingredient:

Water, Glycerin, Acrylic Acid, Trolamine, Fragrance

Other Information

May discolor certain fabrics

Do not store above 105F